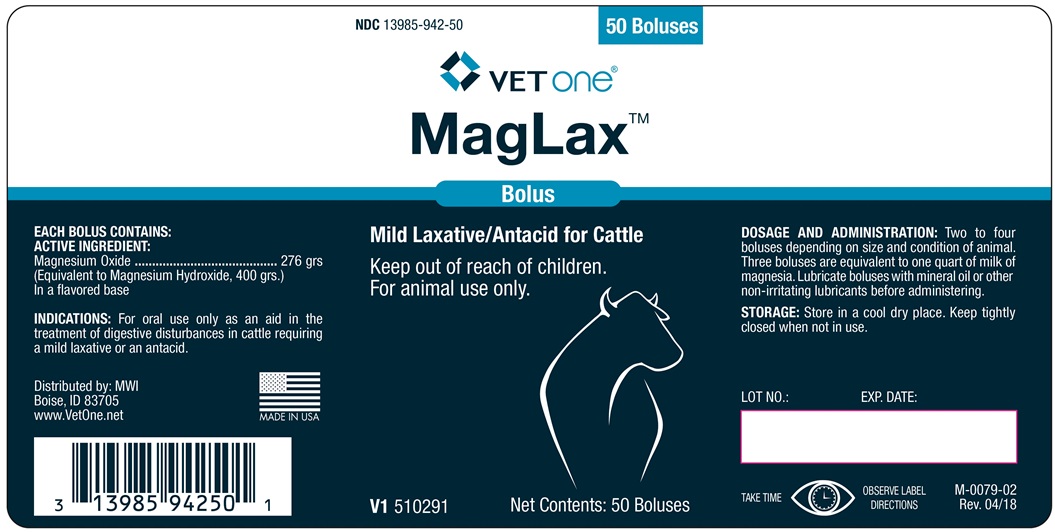 DRUG LABEL: MagLax
NDC: 13985-942 | Form: TABLET
Manufacturer: MWI Veterinary Supply, Inc.
Category: animal | Type: OTC ANIMAL DRUG LABEL
Date: 20180425

ACTIVE INGREDIENTS: MAGNESIUM OXIDE 17.9 g/1 1
INACTIVE INGREDIENTS: SODIUM STARCH GLYCOLATE TYPE A CORN; MAGNESIUM STEARATE; STARCH 1500, PREGELATINIZED; WATER

Magnalax Bolus

INDICATIONS AND USAGE

Mild Laxative/Antacid for Cattle

Keep out of reach of children.

For animal use only.

Indications:

For oral use only as an aid in the treatment of digestive disturbances in cattle requiring a mild laxative or an antacid.

EACH BOLUS CONTAINS

ACTIVE INGREDIENT:

Magnesium Oxide ................. 276 gr

(Equivalent to Magnesium Hydroxide, 400 grs.)

In a flavored base

DOSAGE AND ADMINISTRATION

Two to four boluses depending on size and condition of animal. Three boluses are equivalent to one quart of milk of magnesia. Lubricate boluses with mineral oil or other non-irritating lubricants before administering.

STORAGE

Store in a cool dry place. Keep tightly closed with not in use.

TAKE TIME OBSERVE LABEL DIRECTIONS